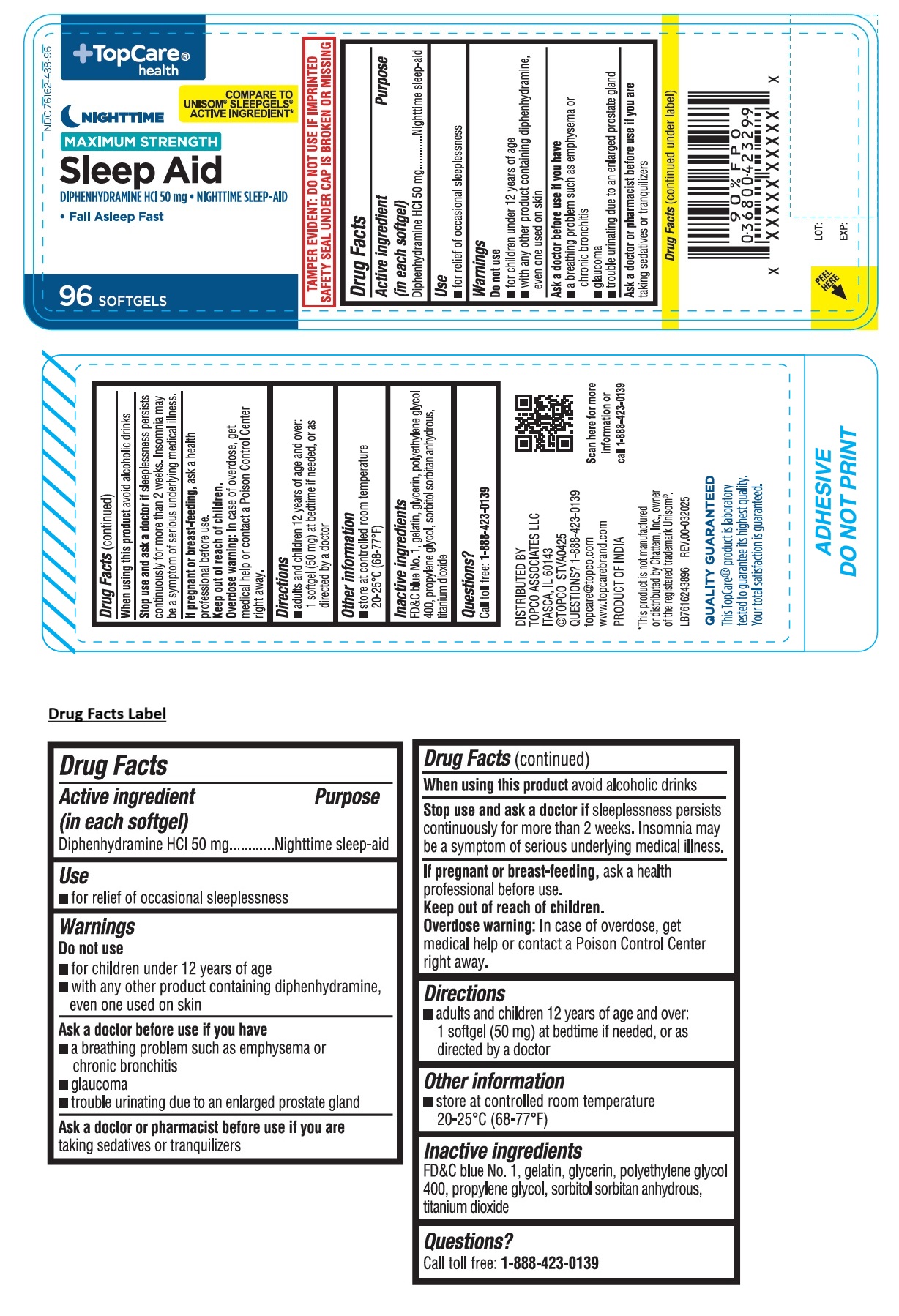 DRUG LABEL: TopCare health NIGHTTIME MAXIMUM STRENGTH Sleep Aid
NDC: 76162-438 | Form: CAPSULE, LIQUID FILLED
Manufacturer: Topco Associates LLC
Category: otc | Type: HUMAN OTC DRUG LABEL
Date: 20250801

ACTIVE INGREDIENTS: DIPHENHYDRAMINE HYDROCHLORIDE 50 mg/1 1
INACTIVE INGREDIENTS: FD&C BLUE NO. 1; GELATIN, UNSPECIFIED; GLYCERIN; POLYETHYLENE GLYCOL 400; PROPYLENE GLYCOL; SORBITOL; SORBITAN; TITANIUM DIOXIDE

TopCare® health NIGHTTIME MAXIMUM STRENGTH Sleep Aid

Active ingredient (in each softgel)

Diphenhydramine HCl 50 mg

Purpose

Nighttime sleep-aid

Use

• for relief of occasional sleeplessness

Warnings

Do not use
• for children under 12 years of age
• with any other product containing diphenhydramine, even one used on skin

Ask a doctor before use if you have
• a breathing problem such as emphysema or chronic bronchitis
• glaucoma
• trouble urinating due to an enlarged prostate gland

Ask a doctor or pharmacist before use if you are taking sedatives or tranquilizers

When using this product avoid alcoholic drinks

Stop use and ask a doctor if sleeplessness persist continuously for more than 2 weeks. Insomnia may be a symptom of serious underlying medical illness.

If pregnant or breast-feeding, ask a health professional before use.

Keep out of reach of children. Overdose warning:
In case of overdose, get medical help or contact a Poison Control Center right away.

Directions

• adults and children 12 years of age and over: 1 softgel (50 mg) at bedtime if needed, or as directed by a doctor

Other information

• store at controlled room temperature 20–25°C (68–77°F)

Inactive ingredients

FD&C blue No. 1, gelatin, glycerin, polyethylene glycol 400, propylene glycol, sorbitol sorbitan anhydrous, titanium dioxide

Questions?

Call toll-free: 1-888-423-0139

®COMPARE TO UNISOM® SLEEPGELS® ACTIVE INGREDIENT*

• Fall Asleep Fast

TAMPER EVIDENT: DO NOT USE IF IMPRINTED SAFETY SEAL UNDER CAP IS BROKEN OR MISSING

DISTRIBUTED BY
TOPCO ASSOCIATES LLC
ITASCA, IL 60143
©TOPCO STVA0425
topcare@topco.com
www.topcarebrand.com
PRODUCT OF INDIA

*This product is not manufactured or distributed by Chattem, Inc., owner of the registered trademark Unisom® .

QUALITY GUARANTEED

This TopCare® product is laboratory tested to guarantee its highest quality. Your total satisfaction is guaranteed.